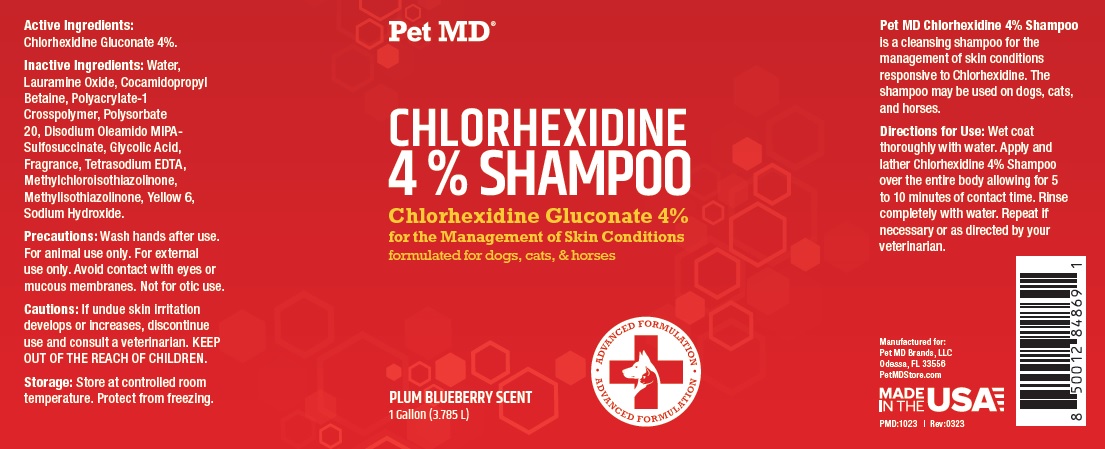 DRUG LABEL: Pet MD CHLORHEXIDINE 4%
NDC: 86090-010 | Form: SHAMPOO
Manufacturer: Pet MD Brands, LLC
Category: animal | Type: OTC ANIMAL DRUG LABEL
Date: 20230908

ACTIVE INGREDIENTS: CHLORHEXIDINE GLUCONATE 4 g/100 mL
INACTIVE INGREDIENTS: WATER; LAURAMINE OXIDE; COCAMIDOPROPYL BETAINE; POLYACRYLATE-1 CROSSPOLYMER; POLYSORBATE 20; DISODIUM OLEAMIDO MIPA-SULFOSUCCINATE; GLYCOLIC ACID; EDETATE SODIUM; METHYLCHLOROISOTHIAZOLINONE; METHYLISOTHIAZOLINONE; FD&C YELLOW NO. 6; SODIUM HYDROXIDE

Pet MD® CHLORHEXIDINE 4% SHAMPOO

Active Ingredients:

Chlorhexidine Gluconate 4%.

INDICATIONS AND USAGE

Pet MD Chlorhexidine 4% Shampoo is a cleansing shampoo for the management of skin conditions responsive to Chlorhexidine. The shampoo may be used on dogs, cats, and horses.

Inactive Ingredients:

Water, Lauramine Oxide, Cocamidopropyl Betaine, Polyacrylate-1 Crosspolymer, Polysorbate 20, Disodium Oleamido MIPA-Sulfosuccinate, Glycolic Acid, Fragrance, Tetrasodium EDTA, Methylchloroisothiazolinone, Methylisothiazolinone, Yellow 6, Sodium Hydroxide.

Precautions:

Wash hands after use. For animal use only. For external use only. Avoid contact with eyes or mucous membranes. Not for otic use.

Cautions:

If undue skin irritation develops or increases, discontinue use and consult a veterinarian. KEEP OUT OF THE REACH OF CHILDREN.

Storage:

Store at controlled room temperature. Protect from freezing.

Directions for Use:

Wet coat thoroughly with water. Apply and lather Chlorhexidine 4% Shampoo over the entire body allowing for 5 to 10 minutes of contact time. Rinse completely with water. Repeat if necessary or as directed by your veterinarian.

formulated for dogs, cats, & horses

ADVANCED FORMULATION

PLUM BLUEBERRY SCENT

Manufactured for:
Pet MD Brands, LLC
Odessa, FL 33556
PetMDStore.com

MADE IN THE USA